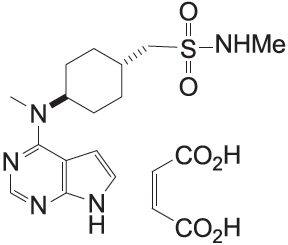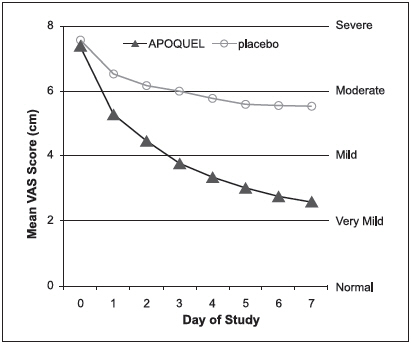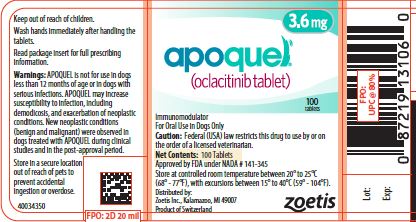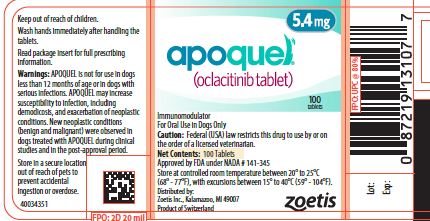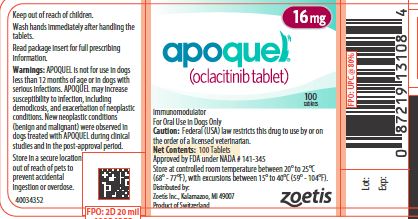 DRUG LABEL: Apoquel
NDC: 54771-8721 | Form: TABLET, COATED
Manufacturer: Zoetis Inc.
Category: animal | Type: PRESCRIPTION ANIMAL DRUG LABEL
Date: 20210728

ACTIVE INGREDIENTS: OCLACITINIB MALEATE 3.6 mg/1 1

apoquel

apoquel®
(oclacitinib tablet)

Immunomodulator

For oral use in dogs only

Caution

Federal (USA) Law restricts this drug to use by or on the order of a licensed veterinarian.

Description

APOQUEL (oclacitinib maleate) is a synthetic Janus Kinase (JAK) inhibitor. The chemical composition of APOQUEL is N-methyl[trans-4-(methyl-7H-pyrrolo[2,3-d]pyrimidin-4-ylamino)cyclohexyl]methanesulfonamide (2Z)-2-butenedioate.

The chemical structure of oclacitinib maleate is:

Indications

Control of pruritus associated with allergic dermatitis and control of atopic dermatitis in dogs at least 12 months of age.

Dosage and Administration

The dose of APOQUEL (oclacitinib maleate) tablets is 0.18 to 0.27 mg oclacitinib/lb (0.4 to 0.6 mg oclacitinib/kg) body weight, administered orally, twice daily for up to 14 days, and then administered once daily for maintenance therapy. APOQUEL may be administered with or without food.

Dosing Chart
Weight Range (in lb) |  | Weight Range (in Kg) |  |  | Number of Tablets to be Administered
Low | High | Low | High |  | 3.6 mg Tablets | 5.4 mg Tablets | 16 mg Tablets
6.6 | 9.9 | 3.0 | 4.4 |  | 0.5 | - | -
10.0 | 14.9 | 4.5 | 5.9 |  | - | 0.5 | -
15.0 | 19.9 | 6.0 | 8.9 |  | 1 | - | -
20.0 | 29.9 | 9.0 | 13.4 |  | - | 1 | -
30.0 | 44.9 | 13.5 | 19.9 |  | - | - | 0.5
45.0 | 59.9 | 20.0 | 26.9 |  | - | 2 | -
60.0 | 89.9 | 27.0 | 39.9 |  | - | - | 1
90.0 | 129.9 | 40.0 | 54.9 |  | - | - | 1.5
130.0 | 175.9 | 55.0 | 80.0 |  | - | - | 2

Warnings

APOQUEL is not for use in dogs less than 12 months of age (see Animal Safety).

APOQUEL modulates the immune system.
APOQUEL is not for use in dogs with serious infections.
APOQUEL may increase susceptibility to infection, including demodicosis, and exacerbation of neoplastic conditions (see Precautions, Adverse Reactions, Post-Approval Experience and Animal Safety).

New neoplastic conditions (benign and malignant) were observed in dogs treated with APOQUEL during clinical studies and have been reported in the post-approval period (see Adverse Reactions and Post-Approval Experience).

Consider the risks and benefits of treatment prior to initiating APOQUEL in dogs with a history of recurrent serious infections or recurrent demodicosis or neoplasia (see Adverse Reactions, Post-Approval Experience, and Animal Safety).

Keep APOQUEL in a secure location out of reach of dogs, cats, and other animals to prevent accidental ingestion or overdose.

Human Warnings

This product is not for human use. Keep this and all drugs out of reach of children. For use in dogs only. Wash hands immediately after handling the tablets. In case of accidental eye contact, flush immediately with water or saline for at least 15 minutes and then seek medical attention. In case of accidental ingestion, seek medical attention immediately.

Precautions

Dogs receiving APOQUEL should be monitored for the development of infections, including demodicosis, and neoplasia.

The use of APOQUEL has not been evaluated in combination with glucocorticoids, cyclosporine, or other systemic immunosuppresive agents.

APOQUEL is not for use in breeding dogs, or pregnant or lactating bitches.

Adverse Reactions

Control of Atopic Dermatitis

In a masked field study to assess the effectiveness and safety of oclacitinib for the control of atopic dermatitis in dogs, 152 dogs treated with APOQUEL and 147 dogs treated with placebo (vehicle control) were evaluated for safety. The majority of dogs in the placebo group withdrew from the 112-day study by Day 16. Adverse reactions reported (and percent of dogs affected) during Days 0-16 included diarrhea (4.6% APOQUEL, 3.4% placebo), vomiting (3.9% APOQUEL, 4.1% placebo), anorexia (2.6% APOQUEL, 0% placebo), new cutaneous or subcutaneous lump (2.6% APOQUEL, 2.7% placebo), and lethargy (2.0% APOQUEL, 1.4% placebo). In most cases, diarrhea, vomiting, anorexia, and lethargy spontaneously resolved with continued dosing. Dogs on APOQUEL had decreased leukocytes (neutrophil, eosinophil, and monocyte counts) and serum globulin, and increased cholesterol and lipase compared to the placebo group but group means remained within the normal range. Mean lymphocyte counts were transiently increased at Day 14 in the APOQUEL group.

Dogs that withdrew from the masked field study could enter an unmasked study where all dogs received APOQUEL. Between the masked and unmasked study, 283 dogs received at least one dose of APOQUEL. Of these 283 dogs, two dogs were withdrawn from study due to suspected treatment-related adverse reactions: one dog that had an intense flare-up of dermatitis and severe secondary pyoderma after 19 days of APOQUEL administration, and one dog that developed generalized demodicosis after 28 days of APOQUEL administration. Two other dogs on APOQUEL were withdrawn from study due to suspected or confirmed malignant neoplasia and subsequently euthanized, including one dog that developed signs associated with a heart base mass after 21 days of APOQUEL administration, and one dog that developed a Grade III mast cell tumor after 60 days of APOQUEL administration.

One of the 147 dogs in the placebo group developed a Grade I mast cell tumor and was withdrawn from the masked study. Additional dogs receiving APOQUEL were hospitalized for diagnosis and treatment of pneumonia (one dog), transient bloody vomiting and stool (one dog), and cystitis with urolithiasis (one dog).

In the 283 dogs that received APOQUEL, the following additional clinical signs were reported after beginning APOQUEL (percentage of dogs with at least one report of the clinical sign as a non-pre-existing finding): pyoderma (12.0%), non-specified dermal lumps (12.0%), otitis (9.9%), vomiting (9.2%), diarrhea (6.0%), histiocytoma (3.9%), cystitis (3.5%), anorexia (3.2%), lethargy (2.8%), yeast skin infections (2.5%), pododermatitis (2.5%), lipoma (2.1%), polydipsia (1.4%), lymphadenopathy (1.1%), nausea (1.1%), increased appetite (1.1%), aggression (1.1%), and weight loss (0.7).

Control of Pruritus Associated with Allergic Dermatitis

In a masked field study to assess the effectiveness and safety of oclacitinib for the control of pruritus associated with allergic dermatitis in dogs, 216 dogs treated with APOQUEL and 220 dogs treated with placebo (vehicle control) were evaluated for safety. During the 30-day study, there were no fatalities and no adverse reactions requiring hospital care. Adverse reactions reported (and percent of dogs affected) during Days 0-7 included diarrhea (2.3% APOQUEL, 0.9% placebo), vomiting (2.3% APOQUEL, 1.8% placebo), lethargy (1.8% APOQUEL, 1.4% placebo), anorexia (1.4% APOQUEL, 0% placebo), and polydipsia (1.4% APOQUEL, 0% placebo). In most of these cases, signs spontaneously resolved with continued dosing. Five APOQUEL group dogs were withdrawn from study because of: darkening areas of skin and fur (1 dog); diarrhea (1 dog); fever, lethargy and cystitis (1 dog); an inflamed footpad and vomiting (1 dog); and diarrhea, vomiting, and lethargy (1 dog). Dogs in the APOQUEL group had a slight decrease in mean white blood cell counts (neutrophil, eosinophil, and monocyte counts) that remained within the normal reference range. Mean lymphocyte count for dogs in the APOQUEL group increased at Day 7, but returned to pretreatment levels by study end without a break in APOQUEL administration. Serum cholesterol increased in 25% of APOQUEL group dogs, but mean cholesterol remained within the reference range.

Continuation Field Study

After completing APOQUEL field studies, 239 dogs enrolled in an unmasked (no placebo control), continuation therapy study receiving APOQUEL for an unrestricted period of time. Mean time on this study was 372 days (range 1 to 610 days). Of these 239 dogs, one dog developed demodicosis following 273 days of APOQUEL administration. One dog developed dermal pigmented viral plaques following 266 days of APOQUEL administration. One dog developed a moderately severe bronchopneumonia after 272 days of APOQUEL administration; this infection resolved with antimicrobial treatment and temporary discontinuation of APOQUEL. One dog was euthanized after developing abdominal ascites and pleural effusion of unknown etiology after 450 days of APOQUEL administration. Six dogs were euthanized because of suspected malignant neoplasms: including thoracic metastatic, abdominal metastatic, splenic, frontal sinus, and intracranial neoplasms, and transitional cell carcinoma after 17, 120, 175, 49, 141, and 286 days of APOQUEL administration, respectively. Two dogs each developed a Grade II mast cell tumor after 52 and 91 days of APOQUEL administration, respectively. One dog developed low grade B-cell lymphoma after 392 days of APOQUEL administration. Two dogs each developed an apocrine gland adenocarcinoma (one dermal, one anal sac) after approximately 210 and 320 days of APOQUEL administration, respectively. One dog developed a low grade oral spindle cell sarcoma after 320 days of APOQUEL administration.

Post-Approval Experience (2020): The following adverse events are based on post-approval adverse drug experience reporting for APOQUEL. Not all adverse events are reported to FDA/CVM. It is not always possible to reliably estimate the adverse event frequency or establish a causal relationship to product exposure using these data.

The following adverse events reported in dogs are listed in decreasing order of reporting frequency.

Vomiting, lethargy, anorexia, diarrhea, elevated liver enzymes, dermatitis (i.e. crusts, pododermatitis, pyoderma), seizures, polydipsia, and demodicosis.

Benign, malignant, and unclassified neoplasms, dermal masses (including papilomas and histiocytomas), lymphoma and other cancers have been reported.

Death (including euthanasia) has been reported.

Contact Information:

To report suspected adverse events, for technical assistance or to obtain a copy of the Safety Data Sheet, contact Zoetis Inc. at 1-888-963-8471 or www.zoetis.com.
For additional information about adverse drug experience reporting for animal drugs, contact FDA at 1-888-FDA-VETS or online at www.fda.gov/reportanimalae.

Clinical Pharmacology

Mechanism of action

Oclacitinib inhibits the function of a variety of pruritogenic cytokines and pro-inflammatory cytokines, as well as cytokines involved in allergy that are dependent on JAK1 or JAK3 enzyme activity. It has little effect on cytokines involved in hematopoiesis that are dependent on JAK2. Oclacitinib is not a corticosteroid or an antihistamine.

Pharmacokinetics

In dogs, oclacitinib maleate is rapidly and well absorbed following oral administration, with mean time to peak plasma concentrations (Tmax) of less than 1 hour. Following oral administration of 0.4-0.6 mg oclacitinib/kg to 24 dogs, the mean (90% confidence limits [CL]) maximum concentration (Cmax) was 324 (281, 372) ng/mL and the mean area under the plasma concentration-time curve from 0 and extrapolated to infinity (AUC0-inf) was 1890 (1690, 2110) ng∙hr/mL. The prandial state of dogs does not significantly affect the rate or extent of absorption. The absolute bioavailability of oclacitinib maleate was 89%.

Oclacitinib has low protein binding with 66.3-69.7% bound in fortified canine plasma at nominal concentrations ranging from 10-1000 ng/mL. The apparent mean (95% CL) volume of distribution at steady-state was 942 (870, 1014) mL/kg body weight.

Oclacitinib is metabolized in the dog to multiple metabolites and one major oxidative metabolite was identified in plasma and urine. Overall the major clearance route is metabolism with minor contributions from renal and biliary elimination. Inhibition of canine cytochrome P450 enzymes by oclacitinib is minimal; the inhibitory concentrations (IC50s) are 50 fold greater than the observed Cmax values at the use dose.

Mean (95% CL) total body oclacitinib clearance from plasma was low – 316 (237, 396) mL/h/kg body weight (5.3 mL/min/kg body weight). Following IV and PO administration, the terminal t1/2 appeared similar with mean values of 3.5 (2.2, 4.7) and 4.1 (3.1, 5.2) hours, respectively.

Effectiveness

Control of Atopic Dermatitis

A double-masked, 112-day, controlled study was conducted at 18 U.S. veterinary hospitals. The study enrolled 299 client-owned dogs with atopic dermatitis. Dogs were randomized to treatment with APOQUEL (152 dogs: tablets administered at a dose of 0.4-0.6 mg/kg per dose twice daily for 14 days and then once daily) or placebo (147 dogs: vehicle control, tablets administered on the same schedule). During the study, dogs could not be treated with other drugs that could affect the assessment of effectiveness, such as corticosteroids, anti-histamines, or cyclosporine. Treatment success for pruritus for each dog was defined as at least a 2 cm decrease from baseline on a 10 cm visual analog scale (VAS) in pruritus, assessed by the Owner, on Day 28. Treatment success for skin lesions was defined as a 50% decrease from the baseline Canine Atopic Dermatitis Extent and Severity Index (CADESI) score, assessed by the Veterinarian, on Day 28. The estimated proportion of dogs with Treatment Success in Owner-assessed pruritus VAS score and in Veterinarian-assessed CADESI score was greater and significantly different for the APOQUEL group compared to the placebo group.

Estimated Proportion of Dogs with Treatment Success, Atopic Dermatitis
Effectiveness Parameter | APOQUEL | Placebo | P-value
Owner-Assessed Pruritus VAS | 0.66 (n = 131) | 0.04 (n = 133) | p<0.0001
Veterinarian-Assessed CADESI | 0.49 (n = 134) | 0.04 (n = 134) | p<0.0001

Compared to the placebo group, mean Owner-assessed pruritus VAS scores (on Days 1, 2, 7, 14, and 28) and Veterinarian-assessed CADESI scores (on Days 14 and 28) were lower (improved) in dogs in the APOQUEL group. By Day 30, 86% (127/147) of the placebo group dogs and 15% (23/152) of the APOQUEL group dogs withdrew from the masked study because of worsening clinical signs, and had the option to enroll in an unmasked study and receive APOQUEL. For dogs that continued APOQUEL treatment beyond one month, the mean Owner-assessed pruritus VAS scores and Veterinarian-assessed CADESI scores continued to improve through study end at Day 112.

Control of Pruritus Associated with Allergic Dermatitis

A double-masked, 30-day, controlled study was conducted at 26 U.S. veterinary hospitals. The study enrolled 436 client-owned dogs with a history of allergic dermatitis attributed to one or more of the following conditions: atopic dermatitis, flea allergy, food allergy, contact allergy, and other/unspecified allergic dermatitis. Dogs were randomized to treatment with APOQUEL (216 dogs: tablets administered at a dose of 0.4-0.6 mg/kg twice daily) or placebo (220 dogs: vehicle control, tablets administered twice daily). During the study, dogs could not be treated with other drugs that could affect the assessment of pruritus or dermal inflammation such as corticosteroids, anti-histamines, or cyclosporine. Treatment success for each dog was defined as at least a 2 cm decrease from baseline on a 10 cm visual analog scale (VAS) in pruritus, assessed by the Owner, on at least 5 of the 7 evaluation days. The estimated proportion of dogs with Treatment Success was greater and significantly different for the APOQUEL group compared to the placebo group.

Owner-Assessed Pruritus VAS Treatment Success, Allergic Dermatitis
Effectiveness Parameter | APOQUEL (n = 203) | Placebo (n = 204) | P-value
Estimated Proportion of Dogs with Treatment Success | 0.67 | 0.29 | p<0.0001

After one week of treatment, 86.4% of APOQUEL group dogs compared with 42.5% of placebo group dogs had achieved a 2 cm reduction on the 10 cm Owner-assessed pruritus VAS. On each of the 7 days, mean Owner-assessed pruritus VAS scores were lower in dogs in the APOQUEL group (See Figure 1). Veterinarians used a 10 cm VAS scale to assess each dog's dermatitis. After one week of treatment, the mean Veterinarian-assessed VAS dermatitis score for the dogs in the APOQUEL group was lower at 2.2 cm (improved from a baseline value of 6.2 cm) compared with the placebo group mean score of 4.9 cm (from a baseline value of 6.2 cm). For dogs that continued APOQUEL treatment beyond one week, the Veterinarian-assessed dermatitis scores continued to improve through study end at Day 30.

Figure 1: Owner Assessed Pruritus VAS Scores by treatment for Days 0-7

Animal Safety

Margin of Safety in 12 Month Old Dogs

Oclacitinib maleate was administered to healthy, one-year-old Beagle dogs twice daily for 6 weeks, followed by once daily for 20 weeks, at 0.6 mg/kg (1X maximum exposure dose, 8 dogs), 1.8 mg/kg (3X, 8 dogs), and 3.0 mg/kg (5X, 8 dogs) oclacitinib for 26 weeks. Eight dogs received placebo (empty gelatin capsule) at the same dosage schedule. Clinical observations that were considered likely to be related to oclacitinib maleate included papillomas and a dose-dependent increase in the number and frequency of interdigital furunculosis (cysts) on one or more feet during the study. Additional clinical observations were primarily related to the interdigital furunculosis and included dermatitis (local alopecia, erythema, abrasions, scabbing/crusts, and edema of feet) and lymphadenopathy of peripheral nodes. Microscopic findings considered to be oclacitinib maleate-related included decreased cellularity (lymphoid) in Gut-Associated Lymphoid Tissue (GALT), spleen, thymus, cervical and mesenteric lymph node; and decreased cellularity of sternal and femoral bone marrow. Lymphoid hyperplasia and chronic active inflammation was seen in lymph nodes draining feet affected with interdigital furunculosis. Five oclacitinib maleate-treated dogs had microscopic evidence of mild interstitial pneumonia.

Clinical pathology findings considered to be oclacitinib maleate-related included mild, dose-dependent reduction in hemoglobin, hematocrit, and reticulocyte counts during the twice daily dosing period with decreases in the leukocyte subsets of lymphocytes, eosinophils, and basophils. Total proteins were decreased over time primarily due to the albumin fraction.

Vaccine Response Study

An adequate immune response (serology) to killed rabies (RV), modified live canine distemper virus (CDV), and modified live canine parvovirus (CPV) vaccination was achieved in eight 16-week old vaccine naïve puppies that were administered oclacitinib maleate at 1.8 mg/kg oclacitinib (3X maximum exposure dose) twice daily for 84 days. For modified live canine parainfluenza virus (CPI), < 80% (6 of 8) of the dogs achieved adequate serologic response. Clinical observations that were considered likely to be related to oclacitinib maleate treatment included enlarged lymph nodes, interdigital furunculosis, cysts, and pododermatitis. One oclacitinib maleate-treated dog (26-weeks-old) was euthanized on Day 74 after physical examination revealed the dog to be febrile, lethargic, with pale mucous membranes and frank blood in stool. Necropsy revealed pneumonia of short duration and evidence of chronic lymphadenitis of mesenteric lymph nodes. During the three month recovery phase to this study, one oclacitinib maleate-treated dog (32-weeks old) was euthanized on Day 28 due to clinical signs which included enlarged prescapular lymph nodes, bilateral epiphora, lethargy, mild dyspnea, and fever. The dog showed an elevated white blood cell (WBC) count. Necropsy revealed lesions consistent with sepsis secondary to immunosuppression. Bone marrow hyperplasia was consistent with response to sepsis.

Margin of Safety in 6 Month Old Dogs

A margin of safety study in 6-month-old dogs was discontinued after four months due to the development of bacterial pneumonia and generalized demodex mange infections in dogs in the high dose (3X and 5X) treatment groups, dosed at 1.8 and 3.0 mg/kg oclacitinib twice daily, for the entire study.

Storage Conditions

APOQUEL should be stored at controlled room temperature between 20° to 25°C (68° to 77°F) with excursions between 15° to 40°C (59° to 104°F).

How Supplied

APOQUEL tablets contain 3.6 mg, 5.4 mg, or 16 mg of oclacitinib as oclacitinib maleate per tablet. Each strength tablets are packaged in 100 and 250 count bottles. Each tablet is scored and marked with AQ and either an S, M, or L that correspond to the different tablet strengths on both sides.

Approved by FDA under NADA # 141-345
zoetis
Distributed by:
Zoetis Inc.
Kalamazoo, MI 49007
Revised: December 2020
40033180